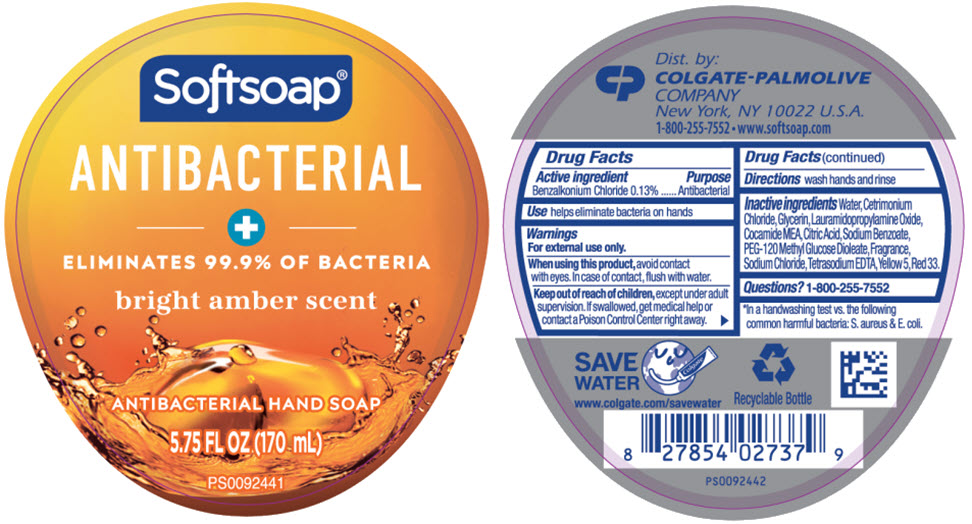 DRUG LABEL: Bright Amber Antibacterial
NDC: 35000-760 | Form: LIQUID
Manufacturer: Colgate-Palmolive Company
Category: otc | Type: HUMAN OTC DRUG LABEL
Date: 20251211

ACTIVE INGREDIENTS: BENZALKONIUM CHLORIDE 1.33 mg/1 mL
INACTIVE INGREDIENTS: WATER; CETRIMONIUM CHLORIDE; GLYCERIN; LAURAMIDOPROPYLAMINE OXIDE; COCO MONOETHANOLAMIDE; ANHYDROUS CITRIC ACID; SODIUM BENZOATE; PEG-120 METHYL GLUCOSE DIOLEATE; SODIUM CHLORIDE; EDETATE SODIUM; FD&C YELLOW NO. 5; D&C RED NO. 33

Bright Amber Antibacterial

Drug Facts

Active ingredient

Benzalkonium Chloride 0.13%

Purpose

Antibacterial

Use

helps eliminate bacteria on hands

Warnings

For external use only.

When using this product, avoid contact with eyes. In case of contact, flush with water.

Keep out of reach of children, except under adult supervision. If swallowed, get medical help or contact a Poison Control Center right away.

Directions

wash hands and rinse

Inactive ingredients

Water, Cetrimonium Chloride, Glycerin, Lauramidopropylamine Oxide, Cocamide MEA, Citric Acid, Sodium Benzoate, PEG-120 Methyl Glucose Dioleate, Fragrance, Sodium Chloride, Tetrasodium EDTA, Yellow 5, Red 33.

Questions?

1-800-255-7552

Dist. by:
COLGATE-PALMOLIVE
COMPANY
New York, NY 10022 U.S.A.

PRINCIPAL DISPLAY PANEL - 170 mL Bottle Label

Softsoap®

ANTIBACTERIAL

+

ELIMINATES 99.9% OF BACTERIA

bright amber scent

ANTIBACTERIAL HAND SOAР

5.75 FL OZ (170 mL)

PS0092441